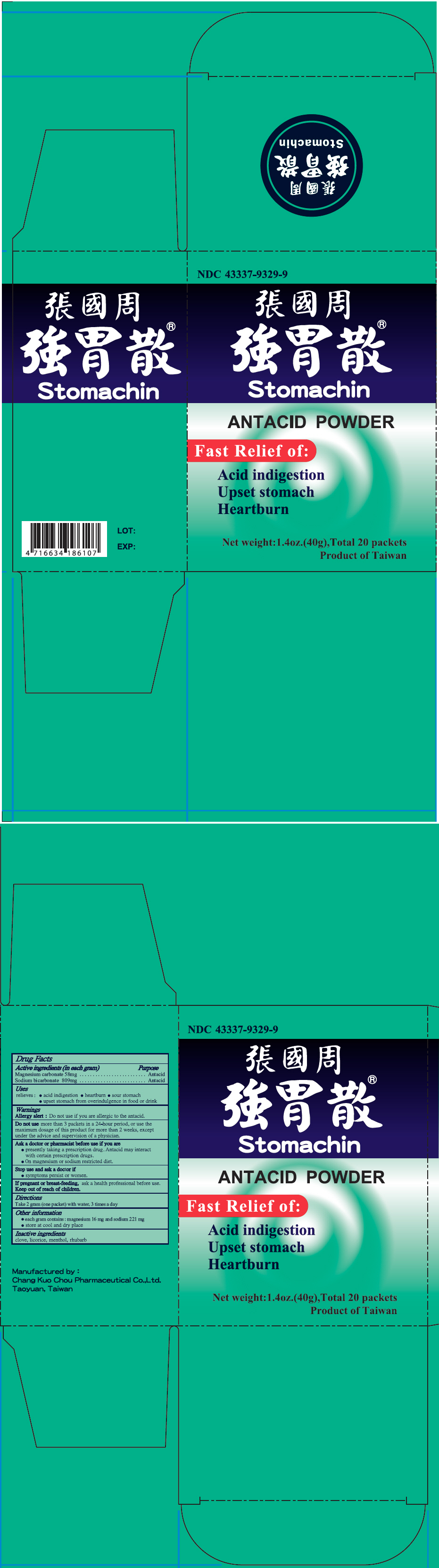 DRUG LABEL: Stomachin Antacid
NDC: 43337-9329 | Form: POWDER
Manufacturer: Chang Kuo Chou Pharmaceutical Co., Ltd.
Category: otc | Type: HUMAN OTC DRUG LABEL
Date: 20250919

ACTIVE INGREDIENTS: MAGNESIUM CARBONATE 58 mg/1 g; SODIUM BICARBONATE 809 mg/1 g
INACTIVE INGREDIENTS: CLOVE 29 mg/1 g; LICORICE 86 mg/1 g; MENTHOL, UNSPECIFIED FORM 4 mg/1 g; RHUBARB 14 mg/1 g

Stomachin®

Drug Facts

ACTIVE INGREDIENT

Active ingredients (in each gram) | Purpose
Magnesium carbonate 58mg | Antacid
Sodium bicarbonate 809mg | Antacid

Uses

relieves:

- acid indigestion
- heartburn
- sour stomach
- upset stomach from overindulgence in food or drink

Warnings

Allergy alert

Do not use if you are allergic to the antacid.

DO NOT USE

Do not usemore than 3 packets in a 24-hour period, or use the maximum dosage of this product for more than 2 weeks, except under the advice and supervision of a physician.

Ask a doctor or pharmacist before use if you are

- presently taking a prescription drug. Antacid may interact with certain prescription drugs.
- On magnesium or sodium restricted diet.

Stop use and ask a doctor if

- symptoms persist or worsen.

PREGNANCY OR BREAST FEEDING

If pregnant or breast-feeding,ask a health professional before use.

Directions

Take 2 gram (one packet) with water, 3 times a day

Other information

- each gram contains : magnesium 16 mg and sodium 221 mg
- store at cool and dry place

Inactive ingredients

clove, licorice, menthol, rhubarb

Manufactured by :
Chang Kuo Chou Pharmaceutical Co.,Ltd.
Taoyuan, Taiwan

PRINCIPAL DISPLAY PANEL - 40 g Packet Box

NDC 43337-9329-9

Stomachin®

ANTACID POWDER

Fast Relief of:

Acid indigestion
Upset stomach
Heartburn

Net weight: 1.4oz.(40g), Total 20 packets

Product of Taiwan